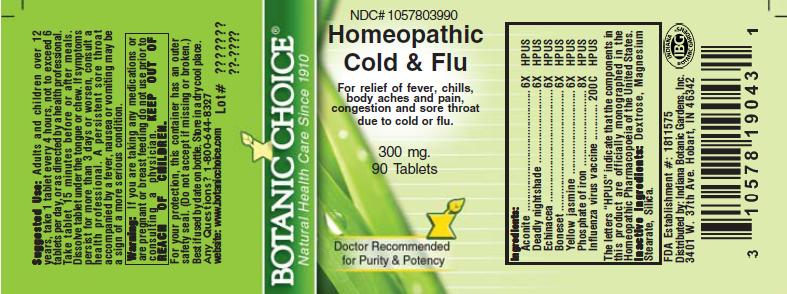 DRUG LABEL: Homeopathic Cold and Flu Formula
NDC: 10578-039 | Form: TABLET
Manufacturer: Indiana Botanic Gardens
Category: homeopathic | Type: HUMAN OTC DRUG LABEL
Date: 20110325

ACTIVE INGREDIENTS: ACONITUM NAPELLUS 6 [hp_X]/1 1; ATROPA BELLADONNA 6 [hp_X]/1 1; ECHINACEA ANGUSTIFOLIA 6 [hp_X]/1 1; EUPATORIUM PERFOLIATUM FLOWERING TOP 6 [hp_X]/1 1; GELSEMIUM SEMPERVIRENS ROOT 6 [hp_X]/1 1; FERRUM PHOSPHORICUM 8 [hp_X]/1 1; HAEMOPHILUS INFLUENZAE TYPE B 200 [hp_C]/1 1
INACTIVE INGREDIENTS: DEXTROSE; MAGNESIUM STEARATE ; SILICON DIOXIDE 

Homeopathic Cold and Flu Formula

ACTIVE INGREDIENT

I n g r e d i e n t s :

Aconite.............................. 6X HPUS
Deadly nightshade..........................................6X HPUS
Purple cone flower.........................6X HPUS
Boneset........................6X HPUS

Yellow jasmine.....................6X HPUS

Phosphate of iron...........................8X HPUS

Influenza virus vaccine........................................200C HPUS

The letters “HPUS” indicate that the components in
this product are officially monographed in the
Homeopathic Pharmacopoeia of the United States.

PURPOSE

For relief of fever, chills, body aches and pain, congestion and sore throat due to cold and flu

KEEP OUT OF
REACH OF CHILDREN.

INDICATIONS AND USAGE

For relief of fever, chills, body aches and pain, congestion and sore throat due to cold and flu

WARNINGS

Warning: If you are taking any medications or
are pregnant or breast feeding do not use prior to
consulting a physician.

DOSAGE AND ADMINISTRATION

Suggested Use: Adults and children over 12
years, take 1 tablet every 4 hours, not to exceed 6 tablets per day, or as directed by a health professional.
Take tablet 15 minutes before or after meals. Dissolve under the tongue or chew. Children under 2 years, consult
a health care professional. If symptoms persist for more than 3 days or worsen, consult a
health professional. A persistent sore throat accompanied by a fever, nausea or vomiting maybe a sign of a more
serious condition.

Inactive Ingredients: Dextrose, Magnesium
Stearate, Silica.

PACKAGE LABEL

NDC# 1057803990

Homeopathic Cold and Flu Formula

For relief of fever, chills, body aches and pain, congestion and sore throat due to cold and flu

300 mg.
90 Tablets

USER SAFETY WARNINGS

For your protection, this container has an outer
safety seal. (Do not accept if missing or broken.)
Best if used by date on bottle. Store in a dry cool place.
Any Questions? 1-800-644-8327
website: www.botanicchoice.com

FDA Establishment #: 1811575

Distributed by: Indiana Botanic Gardens, Inc.
3401 W. 37th Ave. Hobart, IN 46342